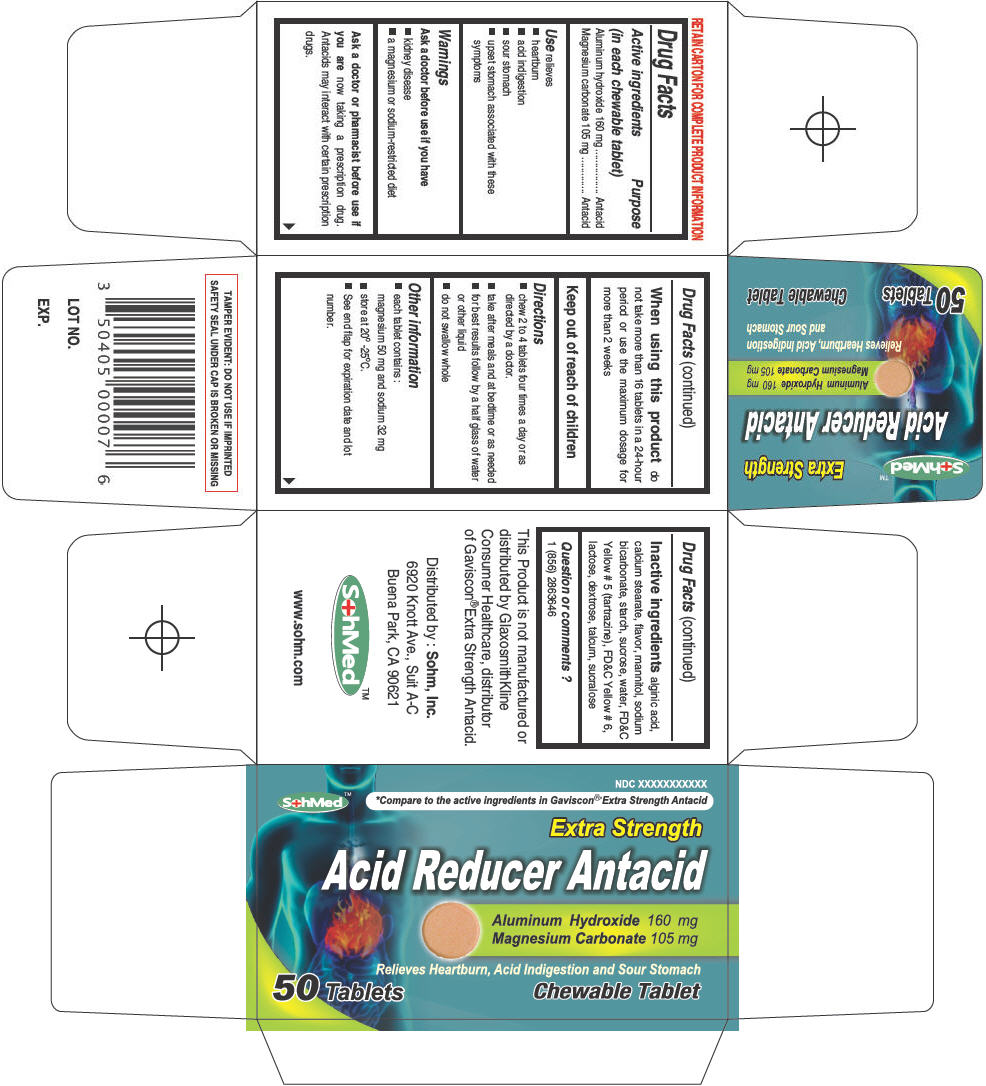 DRUG LABEL: SohMed Acid Reducer
NDC: 50405-002 | Form: TABLET, CHEWABLE
Manufacturer: SOHM Inc.
Category: otc | Type: HUMAN OTC DRUG LABEL
Date: 20130819

ACTIVE INGREDIENTS: ALUMINUM HYDROXIDE 160 mg/1 1; MAGNESIUM CARBONATE 105 mg/1 1
INACTIVE INGREDIENTS: ALGINIC ACID; CALCIUM STEARATE; MANNITOL; SODIUM BICARBONATE; STARCH, CORN; WATER; SUCROSE; FD&C YELLOW No. 5; FD&C YELLOW NO. 6; LACTOSE; DEXTROSE; TALC; SUCRALOSE

SohMed™ Acid Reducer

Drug Facts

ACTIVE INGREDIENT

Active ingredients (in each chewable tablet) | Purpose
Aluminum hydroxide 160 mg | Antacid
Magnesium carbonate 105 mg | Antacid

Use

relieves

- heartburn
- acid indigestion
- sour stomach
- upset stomach associated with these symptoms

Warnings

Ask a doctor before use if you have

- kidney disease
- a magnesium or sodium-restricted diet

Ask a doctor or pharmacist before use if you are now taking a prescription drug. Antacids may interact with certain prescription drugs.

When using this product do not take more than 16 tablets in a 24-hour period or use the maximum dosage for more than 2 weeks

Keep out of reach of children

Directions

- chew 2 to 4 tablets four times a day or as directed by a doctor.
- take after meals and at bedtime or as needed
- for best results follow by a half glass of water or other liquid
- do not swallow whole

Other information

- each tablet contains :
  magnesium 50 mg and sodium 32 mg
- store at 20° -25°C.
- See end flap for expiration date and lot number.

Inactive ingredients

alginic acid, calcium stearate, flavor, mannitol, sodium bicarbonate, starch, sucrose, water, FD&C Yellow # 5 (tartrazine), FD&C Yellow # 6, lactose, dextrose, talcum, sucralose

Question or comments ?

1 (856) 2863646

Distributed by : Sohm, Inc.
6920 Knott Ave., Suit A-C
Buena Park, CA 90621

PRINCIPAL DISPLAY PANEL - 50 Tablet Bottle Carton

NDC XXXXXXXXXXX

SohMed™

*Compare to the active ingredients in Gaviscon® Extra Strength Antacid

Extra Strength

Acid Reducer Antacid

Aluminum Hydroxide 160 mg
Magnesium Carbonate 105 mg

Relieves Heartburn, Acid Indigestion and Sour Stomach

50 Tablets

Chewable Tablet